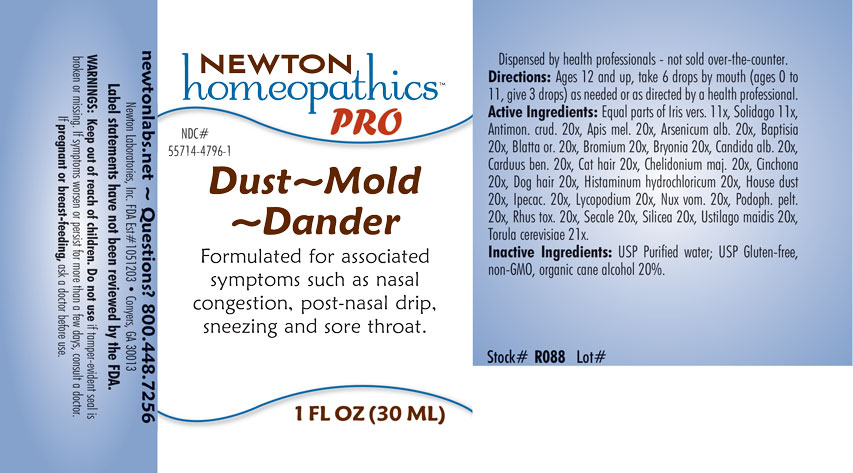 DRUG LABEL: Dust-Mold-Dander
NDC: 55714-4796 | Form: LIQUID
Manufacturer: Newton Laboratories, Inc.
Category: homeopathic | Type: HUMAN OTC DRUG LABEL
Date: 20250210

ACTIVE INGREDIENTS: HOUSE DUST 20 [hp_X]/1 mL; IRIS VERSICOLOR ROOT 11 [hp_X]/1 mL; ANTIMONY TRISULFIDE 20 [hp_X]/1 mL; APIS MELLIFERA 20 [hp_X]/1 mL; ARSENIC TRIOXIDE 20 [hp_X]/1 mL; BAPTISIA TINCTORIA ROOT 20 [hp_X]/1 mL; BLATTA ORIENTALIS 20 [hp_X]/1 mL; BROMINE 20 [hp_X]/1 mL; BRYONIA ALBA ROOT 20 [hp_X]/1 mL; CANDIDA ALBICANS 20 [hp_X]/1 mL; CENTAUREA BENEDICTA 20 [hp_X]/1 mL; FELIS CATUS HAIR 20 [hp_X]/1 mL; CHELIDONIUM MAJUS 20 [hp_X]/1 mL; CINCHONA OFFICINALIS BARK 20 [hp_X]/1 mL; CANIS LUPUS FAMILIARIS HAIR 20 [hp_X]/1 mL; HISTAMINE DIHYDROCHLORIDE 20 [hp_X]/1 mL; IPECAC 20 [hp_X]/1 mL; LYCOPODIUM CLAVATUM SPORE 20 [hp_X]/1 mL; STRYCHNOS NUX-VOMICA SEED 20 [hp_X]/1 mL; PODOPHYLLUM 20 [hp_X]/1 mL; TOXICODENDRON PUBESCENS LEAF 20 [hp_X]/1 mL; CLAVICEPS PURPUREA SCLEROTIUM 20 [hp_X]/1 mL; SILICON DIOXIDE 20 [hp_X]/1 mL; USTILAGO MAYDIS 20 [hp_X]/1 mL; SACCHAROMYCES CEREVISIAE 21 [hp_X]/1 mL; SOLIDAGO VIRGAUREA FLOWERING TOP 11 [hp_X]/1 mL
INACTIVE INGREDIENTS: WATER; ALCOHOL

Dust 4796L

INDICATIONS & USAGE SECTION

Formulated for associated symptoms such as nasal congestions, post-nasal drip, sneezing and sore throat.

DOSAGE & ADMINISTRATION SECTION

Directions: Ages 12 and up, take 6 drops by mouth (ages 0 to 11, give 3 drops) as needed or as directed by a health professional.

OTC - ACTIVE INGREDIENT SECTION

Equal parts of Iris versicolor 11x, Solidago virgaurea 11x, Antimonium crudum 20x, Apis mellifica 20x, Arsenicum album 20x, Baptisia tinctoria 20x, Blatta orientalis 20x, Bromium 20x, Bryonia 20x, Candida albicans 20x, Carduus benedictus 20x, Cat hair 20x, Chelidonium majus 20x, Cinchona officinalis 20x, Dog hair 20x, Histaminum hydrochloricum 20x, House dust 20x, Ipecacuanha 20x, Lycopodium clavatum 20x, Nux vomica 20x, Podophyllum peltatum 20x, Rhus toxicodendron 20x, Secale cornutum 20x, Silicea 20x, Ustilago maidis 20x, Torula cerevisiae 21x.

OTC - PURPOSE SECTION

Formulated for associated symptoms such as nasal congestion, post-nasal drip, sneezing and sore throat.

INACTIVE INGREDIENT SECTION

Inactive Ingredients: USP Purified Water; USP Gluten-free, non-GMO, organic cane alcohol 20%.

QUESTIONS SECTION

newtonlabs.net - Questions? 800.448.7256

Newton Laboratories, Inc. FDA Est # 1051203 Conyers, GA 30013

WARNINGS SECTION

WARNINGS: Keep out of reach of children. Do not use if tamper-evident seal is broken or missing. If symptoms worsen or persist for more than a few days, consult a doctor. If pregnant or breast-feeding, ask a doctor before use.

OTC - PREGNANCY OR BREAST FEEDING SECTION

If pregnant or breast-feeding, ask a doctor before use.

OTC - KEEP OUT OF REACH OF CHILDREN SECTION

Keep out of reach of children.